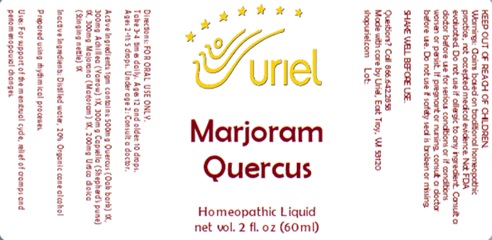 DRUG LABEL: Marjoram Quercus
NDC: 48951-7019 | Form: LIQUID
Manufacturer: Uriel Pharmacy Inc
Category: homeopathic | Type: HUMAN OTC DRUG LABEL
Date: 20241112

ACTIVE INGREDIENTS: SWEET MARJORAM 1 [hp_X]/1 mL; QUERCUS ROBUR WHOLE 1 [hp_X]/1 mL; ACHILLEA MILLEFOLIUM 1 [hp_X]/1 mL; CAPSELLA BURSA-PASTORIS 1 [hp_X]/1 mL; URTICA DIOICA LEAF 1 [hp_X]/1 mL
INACTIVE INGREDIENTS: ALCOHOL; WATER

Marjoram Quercus

INDICATIONS AND USAGE

Directions: FOR ORAL USE ONLY.

DOSAGE AND ADMINISTRATION

Take 3-4 times daily. Ages 12 and older: 10 drops. Ages 2-11: 5 drops. Under age 2: Consult a doctor.

ACTIVE INGREDIENT

Active Ingredients: 1gm contains: 500mg Quercus (Oak bark) 1X, 300mg Achillea (Yarrow) 1X, 300mg Capsella (Shepherd's purse) 1X, 300mg Majorana (Marjoram) 1X, 200mg Urtica dioica (Stinging nettle) 1X

Inactive Ingredients: Distilled water, 20% Organic cane alcohol

Prepared using rhythmical processes.

PURPOSE

Uses: For support of the menstrual cycle, relief of cramps and periomenopausal changes.

KEEP OUT OF REACH OF CHILDREN.

WARNINGS

Warnings: Claims based on traditional homeopathic practice, not accepted medical evidence.
Not FDA evaluated. Do not use if allergic to any ingredient. Consult a doctor before use for serious conditions or if conditions worsen or persist. If pregnant or nursing, consult a doctor before use. Do not use if safety seal is broken or missing.

SHAKE WELL BEFORE USE.

Questions? Call 866.642.2858
Made with care by Uriel, East Troy, WI 53120
shopuriel.com Lot: